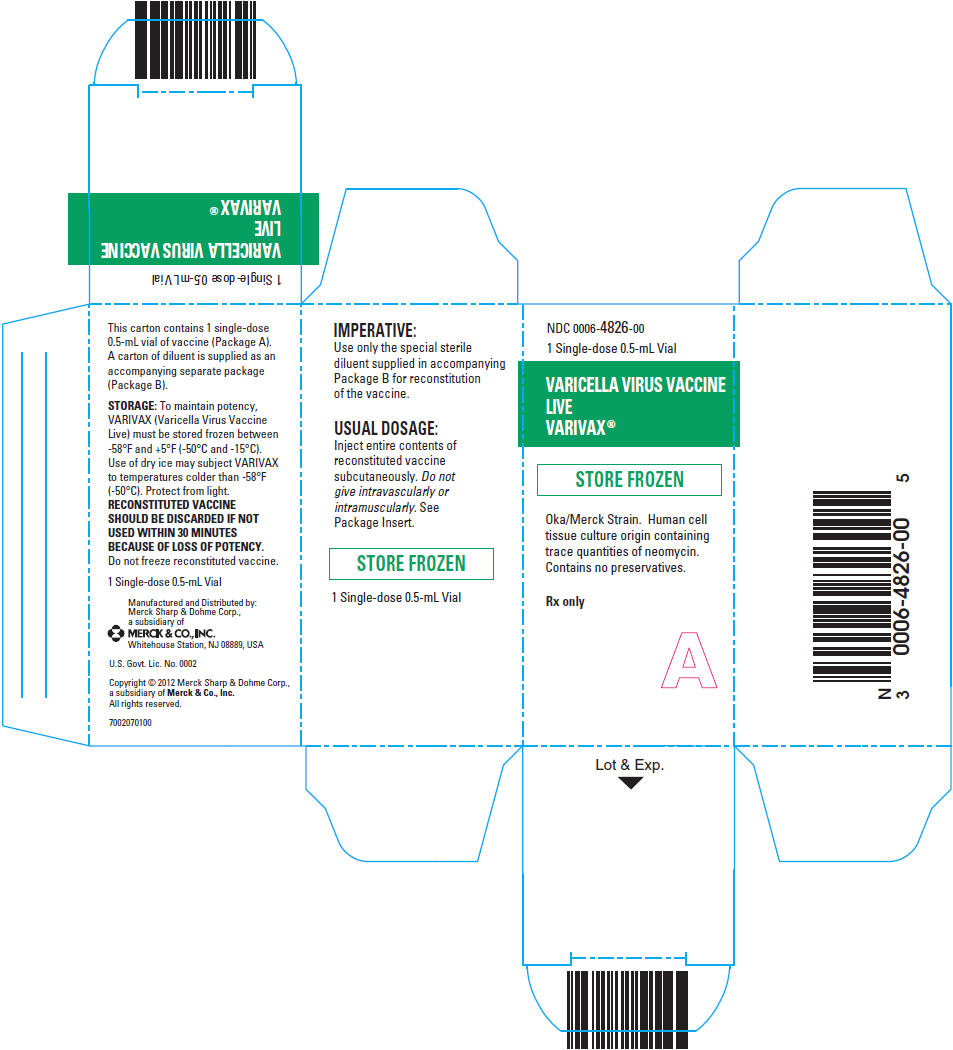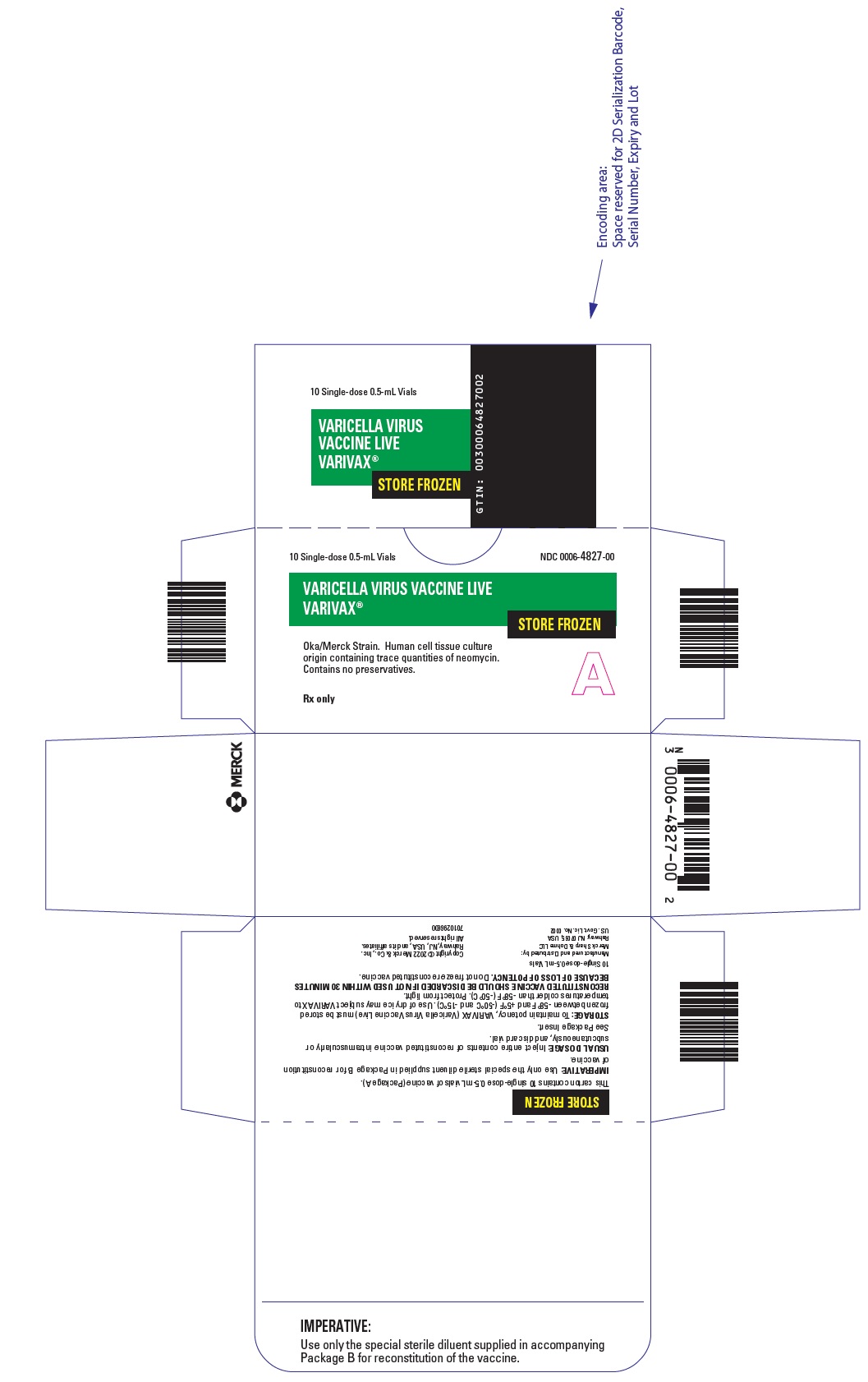 DRUG LABEL: VARIVAX
NDC: 0006-4826 | Form: INJECTION, POWDER, LYOPHILIZED, FOR SUSPENSION
Manufacturer: Merck Sharp & Dohme LLC
Category: other | Type: VACCINE LABEL
Date: 20241108

ACTIVE INGREDIENTS: VARICELLA-ZOSTER VIRUS STRAIN OKA/MERCK LIVE ANTIGEN 1350 [PFU]/0.5 mL
INACTIVE INGREDIENTS: EDETIC ACID; ALBUMIN BOVINE; GELATIN, UNSPECIFIED 12.5 mg/0.5 mL; MONOSODIUM GLUTAMATE 0.5 mg/0.5 mL; NEOMYCIN; POTASSIUM CHLORIDE 0.08 mg/0.5 mL; POTASSIUM PHOSPHATE, MONOBASIC 0.08 mg/0.5 mL; SODIUM CHLORIDE 3.2 mg/0.5 mL; SODIUM PHOSPHATE, DIBASIC, UNSPECIFIED FORM 0.45 mg/0.5 mL; SODIUM PHOSPHATE, MONOBASIC, UNSPECIFIED FORM; SUCROSE 25 mg/0.5 mL

HIGHLIGHTS OF PRESCRIBING INFORMATION

These highlights do not include all the information needed to use VARIVAX safely and effectively. See full prescribing information for VARIVAX.
VARIVAX®
Varicella Virus Vaccine Live
Suspension for intramuscular or subcutaneous injection
Initial U.S. Approval: 1995

RECENT MAJOR CHANGES

Dosage and Administration
Dose and Schedule (2.1) | 02/2023
Reconstitution Instructions (2.2) | 08/2023
Administration (2.3) | 02/2023

1 INDICATIONS AND USAGE

VARIVAX is a vaccine indicated for active immunization for the prevention of varicella in individuals 12 months of age and older. (1)

2 DOSAGE AND ADMINISTRATION

For intramuscular or subcutaneous injection only. (2.1, 2.3)
A single dose is approximately 0.5 mL.

Children (12 months to 12 years of age)

- The first dose is administered at 12 to 15 months of age. (2.1)
- The second dose is administered at 4 to 6 years of age. (2.1)
- There should be a minimum interval of 3 months between doses. (2.1)

Adolescents (≥13 years of age) and Adults

- Two doses are administered at a minimum interval of 4 weeks. (2.1)

3 DOSAGE FORMS AND STRENGTHS

Suspension for injection (approximately 0.5 mL dose) supplied as a lyophilized vaccine to be reconstituted using the accompanying sterile diluent. (2.2, 3, 16)

4 CONTRAINDICATIONS

- History of severe allergic reaction to any component of the vaccine (including neomycin and gelatin) or to a previous dose of varicella vaccine. (4.1)
- Immunosuppression. (4.2)
- Moderate or severe febrile illness. (4.3)
- Active untreated tuberculosis. (4.4)
- Pregnancy. (4.5, 8.1, 17)

5 WARNINGS AND PRECAUTIONS

- Evaluate individuals for immune competence prior to administration of VARIVAX if there is a family history of congenital or hereditary immunodeficiency. (5.1)
- Avoid close contact with high-risk individuals susceptible to varicella because of possible transmission of varicella vaccine virus. (5.3)
- Immune Globulins (IG) and other blood products should not be given concomitantly with VARIVAX. (5.4, 7.2)
- Avoid use of salicylates for 6 weeks following administration of VARIVAX to children and adolescents. (5.5, 7.1)

6 ADVERSE REACTIONS

- Frequently reported (≥10%) adverse reactions in children ages 1 to 12 years include:
  - fever ≥102.0°F (38.9°C) oral: 14.7%
  - injection-site complaints: 19.3% (6.1)
- Frequently reported (≥10%) adverse reactions in adolescents and adults ages 13 years and older include:
  - fever ≥100.0°F (37.8°C) oral: 10.2%
  - injection-site complaints: 24.4% (6.1)
- Other reported adverse reactions in all age groups include:
  - varicella-like rash (injection site)
  - varicella-like rash (generalized) (6.1)

To report SUSPECTED ADVERSE REACTIONS, contact Merck Sharp & Dohme LLC at 1-877-888-4231 or VAERS at 1-800-822-7967 or www.vaers.hhs.gov .

7 DRUG INTERACTIONS

- Reye syndrome has been reported in children and adolescents following the use of salicylates during wild-type varicella infection. (5.5, 7.1)
- Administration of immune globulins and other blood products concurrently with VARIVAX vaccine may interfere with the expected immune response. (5.4, 7.2)
- VARIVAX vaccination may result in a temporary depression of purified protein derivative (PPD) tuberculin skin sensitivity. (7.3)

8 USE IN SPECIFIC POPULATIONS

Pregnancy: Do not administer VARIVAX to females who are pregnant. Pregnancy should be avoided for 3 months following vaccination with VARIVAX. (4.5, 8.1, 17)

FULL PRESCRIBING INFORMATION

1 INDICATIONS AND USAGE

VARIVAX is a vaccine indicated for active immunization for the prevention of varicella in individuals 12 months of age and older.

2 DOSAGE AND ADMINISTRATION

For Intramuscular or Subcutaneous administration only

2.1 Dose and Schedule

A single dose of VARIVAX is approximately 0.5 mL.

Children (12 months to 12 years of age)

The first dose is administered at 12 to 15 months of age but may be given anytime through 12 years of age.

The second dose is administered at 4 to 6 years of age. At least 3 months should elapse between a dose of varicella-containing vaccine and VARIVAX.

At least 1 month should elapse between a dose of measles-containing vaccine and a dose of VARIVAX if the vaccines are not given concurrently [see Clinical Studies (14.1)].

Adolescents (≥13 years of age) and Adults

Two doses of VARIVAX are administered at a minimum interval of 4 weeks [see Clinical Studies (14.1)].

2.2 Reconstitution Instructions

The sterile diluent for VARIVAX is provided in either a vial or prefilled syringe.

Sterile Diluent Vial

Use a sterile syringe free of preservatives, antiseptics, and detergents for each reconstitution and injection of VARIVAX because these substances may inactivate the vaccine virus. When reconstituting the vaccine, use the sterile diluent vial supplied with VARIVAX. The sterile diluent does not contain preservatives or other antiviral substances which might inactivate the vaccine virus.

To reconstitute the vaccine, withdraw the entire volume of the supplied sterile diluent from the vial and slowly inject into the lyophilized vaccine vial. Gently agitate to dissolve completely. Discard if the lyophilized vaccine cannot be dissolved.

Parenteral drug products should be inspected visually for particulate matter and discoloration prior to administration, whenever solution and container permit. Visually inspect the vaccine before and after reconstitution prior to administration. Before reconstitution, the lyophilized vaccine is a white compact crystalline plug. VARIVAX, when reconstituted, is a clear, colorless to pale yellow liquid. Do not use the product if particulates are present or if it appears discolored.

Withdraw and administer the entire volume of the reconstituted vaccine.

Administer VARIVAX immediately after reconstitution. Discard if reconstituted vaccine is not used within 30 minutes.

Do not freeze reconstituted vaccine.

Do not combine VARIVAX with any other vaccine through reconstitution or mixing.

Sterile Diluent Prefilled Syringe

To reconstitute, use the sterile diluent prefilled syringe supplied with the vaccine since it does not contain preservatives or other antiviral substances which might inactivate the vaccine virus.

Attach a needle to the prefilled syringe.

Reconstitute the vaccine by slowly injecting the entire volume of sterile diluent contained in the prefilled syringe into the lyophilized vaccine vial. Gently agitate to dissolve completely. Discard if the lyophilized vaccine cannot be dissolved.

Parenteral drug products should be inspected visually for particulate matter and discoloration prior to administration, whenever solution and container permit. Visually inspect the vaccine before and after reconstitution prior to administration. Before reconstitution, the lyophilized vaccine is a white compact crystalline plug. VARIVAX, when reconstituted, is a clear, colorless to pale yellow liquid. Do not use the reconstituted vaccine if particulates are present or if it appears discolored.

Withdraw and administer the entire volume of the reconstituted vaccine.

Administer VARIVAX immediately after reconstitution. Discard if reconstituted vaccine is not used within 30 minutes.

Do not freeze reconstituted vaccine.

Do not combine VARIVAX with any other vaccine through reconstitution or mixing.

2.3 Administration

Inject the vaccine intramuscularly or subcutaneously.

3 DOSAGE FORMS AND STRENGTHS

VARIVAX is a suspension for injection supplied as a single-dose vial of lyophilized vaccine to be reconstituted using the accompanying sterile diluent [see Dosage and Administration (2.2) and How Supplied/Storage and Handling (16)]. A single dose after reconstitution is approximately 0.5 mL.

4 CONTRAINDICATIONS

4.1 Severe Allergic Reaction

Do not administer VARIVAX to individuals with a history of anaphylactic or severe allergic reaction to any component of the vaccine (including neomycin and gelatin) or to a previous dose of a varicella-containing vaccine.

4.2 Immunosuppression

Do not administer VARIVAX to individuals who are immunodeficient or immunosuppressed due to disease or medical therapy.

Disseminated varicella disease and extensive vaccine-associated rash have been reported in individuals who are immunosuppressed or immunodeficient who were inadvertently vaccinated with a varicella-containing vaccine.

4.3 Moderate or Severe Febrile Illness

Do not administer VARIVAX to individuals with an active febrile illness with fever >101.3°F (>38.5°C).

4.4 Active Untreated Tuberculosis

Do not administer VARIVAX to individuals with active, untreated tuberculosis (TB).

4.5 Pregnancy

Do not administer VARIVAX to individuals who are pregnant or planning on becoming pregnant in the next 3 months. Wild-type varicella is known to cause fetal harm [see Use in Specific Populations (8.1) and Patient Counseling Information (17)].

5 WARNINGS AND PRECAUTIONS

5.1 Family History of Immunodeficiency

Vaccination should be deferred in individuals with a family history of congenital or hereditary immunodeficiency until the individual's immune status has been evaluated and the individual has been found to be immunocompetent.

5.2 Use in HIV-Infected Individuals

The Advisory Committee on Immunization Practices (ACIP) has recommendations on the use of varicella vaccine in HIV-infected individuals.

5.3 Risk of Vaccine Virus Transmission

Post-marketing experience suggests that transmission of varicella vaccine virus (Oka/Merck) resulting in varicella infection including disseminated disease may occur between vaccine recipients (who develop or do not develop a varicella-like rash) and contacts susceptible to varicella including healthy as well as high-risk individuals.

Due to the concern for transmission of vaccine virus, vaccine recipients should attempt to avoid whenever possible close association with susceptible high-risk individuals for up to six weeks following vaccination with VARIVAX. Susceptible high-risk individuals include:

- Immunocompromised individuals;
- Pregnant women without documented history of varicella or laboratory evidence of prior infection;
- Newborn infants of mothers without documented history of varicella or laboratory evidence of prior infection and all newborn infants born at <28 weeks gestation regardless of maternal varicella immunity.

5.4 Immune Globulins and Transfusions

Immune Globulins (IG) and other blood products should not be given concomitantly with VARIVAX [see Drug Interactions (7.2)]. These products may contain antibodies that interfere with vaccine virus replication and decrease the expected immune response.

The ACIP has specific recommendations for intervals between administration of antibody-containing products and live virus vaccines.

5.5 Salicylate Therapy

Avoid use of salicylates (aspirin) or salicylate-containing products in children and adolescents 12 months through 17 years of age for six weeks following vaccination with VARIVAX because of the association of Reye syndrome with salicylate therapy and wild-type varicella infection [see Drug Interactions (7.1)].

6 ADVERSE REACTIONS

6.1 Clinical Trials Experience

Because clinical trials are conducted under widely varying conditions, adverse reaction rates observed in the clinical trials of a vaccine cannot be directly compared to rates in the clinical trials of another vaccine and may not reflect the rates observed in clinical practice. Vaccine-related adverse reactions reported during clinical trials were assessed by the study investigators to be possibly, probably, or definitely vaccine-related and are summarized below.

In clinical trials {1-8}, VARIVAX was administered subcutaneously to over 11,000 healthy children, adolescents, and adults.

In a double-blind, placebo-controlled study among 914 healthy children and adolescents who were serologically confirmed to be susceptible to varicella, the only adverse reactions that occurred at a significantly (p<0.05) greater rate in vaccine recipients than in placebo recipients were pain and redness at the injection site {1}.

Children 1 to 12 Years of Age

One-Dose Regimen in Children

In clinical trials involving healthy children monitored for up to 42 days after a single dose of VARIVAX, the frequency of fever, injection-site complaints, or rashes were reported as shown in Table 1:

Table 1: Fever, Local Reactions, and Rashes (%) in Children 1 to 12 Years of Age 0 to 42 Days After Receipt of a Single Dose of VARIVAX
Reaction |  | N | % Experiencing Reaction | Peak Occurrence During Postvaccination Days
Fever ≥102.0°F (38.9°C) Oral |  | 8827 | 14.7% | 0 to 42
Injection-site complaints |  | 8916 | 19.3% | 0 to 2
 | (pain/soreness, swelling and/or erythema, rash, pruritus, hematoma, induration, stiffness) | 8916 | 19.3% | 0 to 2
Varicella-like rash (injection site) |  | 8916 | 3.4% | 8 to 19
Median number of lesions |  |  | 2
Varicella-like rash (generalized) |  | 8916 | 3.8% | 5 to 26
Median number of lesions |  |  | 5

In addition, adverse events occurring at a rate of ≥1% are listed in decreasing order of frequency: upper respiratory illness, cough, irritability, fatigue, disturbed sleep, diarrhea, loss of appetite, vomiting, otitis, headache, malaise, abdominal pain, other rash, nausea, chills, lymphadenopathy, myalgia, lower respiratory illness, allergic reactions (including allergic rash, hives), stiff neck, arthralgia, itching.

Pneumonitis has been reported rarely (<1%) in children vaccinated with VARIVAX.

Febrile seizures have occurred at a rate of <0.1% in children vaccinated with VARIVAX.

Two-Dose Regimen in Children

Nine hundred eighty-one (981) subjects in a clinical trial received 2 doses of VARIVAX 3 months apart and were actively followed for 42 days after each dose. The 2-dose regimen of varicella vaccine had a safety profile comparable to that of the 1-dose regimen. The overall incidence of injection-site clinical complaints (primarily erythema and swelling) observed in the first 4 days following vaccination was 25.4% Postdose 2 and 21.7% Postdose 1, whereas the overall incidence of systemic clinical complaints in the 42-day follow-up period was lower Postdose 2 (66.3%) than Postdose 1 (85.8%).

Adolescents (13 Years of Age and Older) and Adults

In clinical trials involving healthy adolescents and adults, the majority of whom received two doses of VARIVAX and were monitored for up to 42 days after any dose, the frequencies of fever, injection-site complaints, or rashes are shown in Table 2.

Table 2: Fever, Local Reactions, and Rashes (%) in Adolescents and Adults 0 to 42 Days After Receipt of VARIVAX
Reaction |  | N | % Post Dose 1 | Peak Occurrence in Postvaccination Days | N | % Post Dose 2 | Peak Occurrence in Postvaccination Days
Fever ≥100.0°F (37.8°C) Oral |  | 1584 | 10.2% | 14 to 27 | 956 | 9.5% | 0 to 42
Injection-site complaints |  | 1606 | 24.4% | 0 to 2 | 955 | 32.5% | 0 to 2
 | (soreness, erythema, swelling, rash, pruritus, pyrexia, hematoma, induration, numbness) | 1606 | 24.4% | 0 to 2 | 955 | 32.5% | 0 to 2
Varicella-like rash (injection site) |  | 1606 | 3% | 6 to 20 | 955 | 1% | 0 to 6
Median number of lesions |  |  | 2 |  |  | 2
Varicella-like rash (generalized) |  | 1606 | 5.5% | 7 to 21 | 955 | 0.9% | 0 to 23
Median number of lesions |  |  | 5 |  |  | 5.5

In addition, adverse events reported at a rate of ≥1% are listed in decreasing order of frequency: upper respiratory illness, headache, fatigue, cough, myalgia, disturbed sleep, nausea, malaise, diarrhea, stiff neck, irritability, lymphadenopathy, chills, abdominal pain, loss of appetite, arthralgia, otitis, itching, vomiting, other rashes, lower respiratory illness, allergic reactions (including allergic rash, hives).

In a randomized open-label clinical trial (NCT00432523), conducted in France and Germany, 752 children 12 months through 18 months of age received M-M-R II concomitantly administered with VARIVAX at a separate site, by either the intramuscular (n=374) or subcutaneous (n=378) route. In the overall population, 55.3% were male and the median age was 13.2 months. Local and systemic solicited adverse reactions were recorded by parents or guardians using standardized diary cards. Local solicited reactions were recorded for 4 days after vaccination, and systemic solicited adverse reactions were recorded for 42 days after vaccination. In the event that a participant experienced a rash or a mumps-like illness, parents and/or guardians were instructed to contact the investigator for an examination as soon as possible and no later than 72 hours following onset of symptoms. The nature of any rash was characterized by principal investigator either as measles-like, rubella-like, varicella-like or “other”. Study investigators reviewed the diary card with the participant or participant’s legal guardian 42 days after vaccination to ensure consistency with protocol definitions. Table 3 below presents the frequency of solicited adverse reactions based on the final assessment by the study investigators.

Table 3: Proportion of Participants Reporting Solicited Adverse Reactions Following Vaccination with VARIVAX Concomitantly Administered with M-M-R II, by the Intramuscular or Subcutaneous Route
 | Intramuscular N=374 % | Subcutaneous N=376 %
Solicited local reactions at Varivax injection site (Days 0 to 4) [During the post vaccination monitoring period (0-42 days), eight participants experienced a varicella-like injection-site rash at the VARIVAX injection site. All were reported in the subcutaneous group.]
Erythema [Intensity of injection site reaction: mild or ≤2.5 cm; moderate or >2.5 to ≤5.0 cm; severe or >5.0 cm.] | 8.8 | 16.8
Mild | 8.0 | 12.8
Moderate | 0.5 | 3.7
Severe | 0 | 0
Missing | 0.3 | 0.3
Pain [Intensity of pain: mild: awareness of symptom but easily tolerated; moderate: definitely acting like something is wrong; severe: extremely distressed or unable to do usual activities.] | 7.0 | 8.5
Mild | 4.8 | 7.2
Moderate | 2.1 | 1.3
Severe | 0 | 0
Swelling | 3.2 | 4.8
Mild | 1.6 | 3.5
Moderate | 1.1 | 0.5
Severe | 0 | 0
Missing | 0.5 | 0.8
Solicited systemic adverse reactions (Days 0 to 42)
Measles-like rash (Days 0 to 42) [Testing to distinguish between rash caused by wild-type or vaccine virus was not performed. Reports of measles-, rubella-, and varicella-like rash included 3 reports of measles, 1 report of rubella, and 1 report of varicella, all with onset within 15 days post-vaccination.] | 2.9 | 2.7
Rubella-like rash (Days 0 to 42) | 2.7 | 2.7
Varicella-like rash (Days 0 to 42) | 0.5 | 3.2
Mumps-like illness (Days 0 to 42) | 0 | 0.3
Fever (temperature ≥38.0°C) (Days 0 to 42) [The percentage of fever is defined within the population who had valid temperature measurements. One participant in IM group and two participants in SC group did not have temperature measurements and were excluded from the denominator; resulting in N=374 and N=376, respectively.] , [In the IM Group 92.3% of fevers were documented using the rectal route of measurement and 7.7% of fevers were documented only by the axillary route of measurement. In the SC Group 89.6% of fevers were documented using the rectal route of measurement and 10.4% of fevers were documented only by the axillary route of measurement.] | 66.5 | 66.8
38.0-38.5°C | 20.4 | 22.2
>38.5-39.0°C | 17.4 | 16.6
>39.0-39.5°C | 14.2 | 13.4
>39.5-40.0°C | 11.8 | 11.0
>40.0°C | 2.7 | 3.7
N=total number of participants in the group

Unsolicited adverse events that occurred within 42 days following vaccination were recorded using diary cards supplemented by medical review. Data on unsolicited adverse events were transcribed into the study database during an on-site visit at day 42. The rates and types of reported adverse events (AEs) across groups were similar and included common clinical events that are often reported in the evaluated populations. Serious adverse events occurred at rates of 0.3% and 1% in the intramuscular and subcutaneous groups, respectively. One moderate intensity case of otitis media occurred in a participant in the subcutaneous group was considered related to the vaccination.

Herpes Zoster

Overall, 9454 healthy children (12 months to 12 years of age) and 1648 adolescents and adults (13 years of age and older) have been vaccinated with VARIVAX in clinical trials. Eight cases of herpes zoster have been reported in children during 42,556 person-years of follow-up in clinical trials, resulting in a calculated incidence of at least 18.8 cases per 100,000 person-years. The completeness of this reporting has not been determined. One case of herpes zoster has been reported in the adolescent and adult age group during 5410 person-years of follow-up in clinical trials, resulting in a calculated incidence of 18.5 cases per 100,000 person-years. All 9 cases were mild and without sequelae. Two cultures (one child and one adult) obtained from vesicles were positive for wild-type VZV as confirmed by restriction endonuclease analysis {11}. The long-term effect of VARIVAX on the incidence of herpes zoster, particularly in those vaccinees exposed to wild-type varicella, is unknown at present.

In children, the reported rate of herpes zoster in vaccine recipients appears not to exceed that previously determined in a population-based study of healthy children who had experienced wild-type varicella {12}. The incidence of herpes zoster in adults who have had wild-type varicella infection is higher than that in children.

6.2 Post-Marketing Experience

The following adverse events have been identified during post approval use of VARIVAX. Because the events are reported voluntarily from a population of uncertain size, it is not always possible to reliably estimate their frequency or establish a causal relationship to vaccine exposure.

Body as a Whole

Anaphylaxis (including anaphylactic shock) and related phenomena such as angioneurotic edema, facial edema, and peripheral edema.

Eye Disorders

Necrotizing retinitis (in immunocompromised individuals).

Hemic and Lymphatic System

Aplastic anemia; thrombocytopenia (including idiopathic thrombocytopenic purpura (ITP)).

Infections and Infestations

Varicella (vaccine strain).

Nervous/Psychiatric

Encephalitis; cerebrovascular accident; transverse myelitis; Guillain-Barré syndrome; Bell's palsy; ataxia; non-febrile seizures; aseptic meningitis; meningitis; dizziness; paresthesia; syncope.

Cases of encephalitis or meningitis caused by vaccine strain varicella virus have been reported in immunocompromised and immunocompetent individuals previously vaccinated with VARIVAX months to years after vaccination. Reported cases were commonly associated with preceding or concurrent herpes zoster rash.

Respiratory

Pharyngitis; pneumonia/pneumonitis.

Skin

Stevens-Johnson syndrome; erythema multiforme; Henoch-Schönlein purpura; secondary bacterial infections of skin and soft tissue, including impetigo and cellulitis; wild-type or vaccine strain herpes zoster.

Herpes Zoster

The vaccine virus (Oka/Merck strain) contained in VARIVAX may establish latency of varicella zoster virus in immunocompetent individuals, with the potential for later development of herpes zoster.

7 DRUG INTERACTIONS

7.1 Salicylates

No cases of Reye syndrome have been observed following vaccination with VARIVAX. Vaccine recipients should avoid use of salicylates for 6 weeks after vaccination with VARIVAX, as Reye syndrome has been reported following the use of salicylates during wild-type varicella infection [see Warnings and Precautions (5.5)].

7.2 Immune Globulins and Transfusions

Administration of immune globulins and other blood products concurrently with VARIVAX may interfere with the expected immune response [see Warnings and Precautions (5.4)] {9}. The ACIP has specific recommendations for intervals between administration of antibody-containing products and live virus vaccines.

7.3 Tuberculin Skin Testing

Tuberculin skin testing, with tuberculin purified protein derivative (PPD), may be performed before VARIVAX is administered or on the same day, or at least 4 weeks following vaccination with VARIVAX, as other live virus vaccines may cause a temporary depression of tuberculin skin test sensitivity leading to false negative results.

7.4 Use with Other Vaccines

VARIVAX can be administered concurrently with other live viral vaccines. If not given concurrently, at least 1 month should elapse between a dose of a live attenuated measles virus-containing vaccine and a dose of VARIVAX. In children through the age of 12 years at least 3 months should elapse between administration of 2 doses of a live attenuated varicella virus-containing vaccine. For adolescents and adults, 2 doses of VARIVAX may be separated by 1 month [see Dosage and Administration (2.1)].

VARIVAX may be administered concomitantly with M-M-R II (Measles, Mumps, and Rubella Virus Vaccine Live), Haemophilus influenzae type b conjugate (meningococcal protein conjugate) and hepatitis B (recombinant). Additionally, VARIVAX may be administered concomitantly with inactivated diphtheria-tetanus and acellular pertussis vaccines [see Clinical Studies (14.4)].

8 USE IN SPECIFIC POPULATIONS

8.1 Pregnancy

Risk Summary

VARIVAX is contraindicated for use in pregnant women because the vaccine contains live, attenuated varicella virus, and it is known that wild-type varicella virus, if acquired during pregnancy, can cause congenital varicella syndrome [see Contraindications (4.5) and Patient Counseling Information (17)]. No increased risk for miscarriage, major birth defect or congenital varicella syndrome was observed in a pregnancy exposure registry that monitored outcomes after inadvertent use. There are no relevant animal data.

All pregnancies have a risk of birth defect, loss, or other adverse outcomes. In the US general population, the estimated background risk of major birth defects and miscarriage in clinically recognized pregnancies is 2% to 4%, and 15% to 20%, respectively.

Human Data

A pregnancy exposure registry was maintained from 1995 to 2013 to monitor pregnancy and fetal outcomes following inadvertent administration of VARIVAX. The registry prospectively enrolled 1522 women who received a dose of VARIVAX during pregnancy or within three months prior to conception. After excluding elective terminations (n=60), ectopic pregnancies (n=1) and those lost to follow-up (n=556), there were 905 pregnancies with known outcomes. Of these 905 pregnancies, 271 (30%) were in women who were vaccinated within the three months prior to conception. Miscarriage was reported for 10% of pregnancies (95/905), and major birth defects were reported for 2.6% of live born infants (21/819). These rates of assessed outcomes were consistent with estimated background rates. None of the women who received VARIVAX vaccine delivered infants with abnormalities consistent with congenital varicella syndrome.

8.2 Lactation

Risk Summary

It is not known whether varicella vaccine virus is excreted in human milk. The developmental and health benefits of breastfeeding should be considered along with the mother's clinical need for VARIVAX, and any potential adverse effects on the breastfed child from VARIVAX or from the underlying maternal condition. For preventive vaccines, the underlying maternal condition is susceptibility to disease prevented by the vaccine.

8.4 Pediatric Use

No clinical data are available on safety or efficacy of VARIVAX in children less than 12 months of age.

8.5 Geriatric Use

Clinical studies of VARIVAX did not include sufficient numbers of seronegative subjects aged 65 and over to determine whether they respond differently from younger subjects.

11 DESCRIPTION

VARIVAX [Varicella Virus Vaccine Live] is a preparation of the Oka/Merck strain of live, attenuated varicella virus. The virus was initially obtained from a child with wild-type varicella, then introduced into human embryonic lung cell cultures, adapted to and propagated in embryonic guinea pig cell cultures and finally propagated in human diploid cell cultures (WI-38). Further passage of the virus for varicella vaccine was performed at Research Laboratories of Merck Sharp & Dohme, LLC, Rahway, NJ, USA in human diploid cell cultures (MRC-5) that were free of adventitious agents. This live, attenuated varicella vaccine is a lyophilized preparation containing sucrose, phosphate, glutamate, and processed gelatin as stabilizers.

VARIVAX, when reconstituted as directed, is a sterile preparation for intramuscular or subcutaneous injection. Each approximately 0.5 mL dose contains a minimum of 1350 plaque-forming units (PFU) of Oka/Merck varicella virus when reconstituted and stored at room temperature for a maximum of 30 minutes. Each approximately 0.5 mL dose also contains approximately 24 mg of sucrose, 12.0 mg hydrolyzed gelatin, 3.1 mg of sodium chloride, 0.5 mg of monosodium L-glutamate, 0.44 mg of sodium phosphate dibasic, 0.08 mg of potassium phosphate monobasic, and 0.08 mg of potassium chloride. The product also contains residual components of MRC-5 cells including DNA and protein and trace quantities of sodium phosphate monobasic, EDTA, neomycin and fetal bovine serum. The product contains no preservative.

12 CLINICAL PHARMACOLOGY

12.1 Mechanism of Action

VARIVAX induces both cell-mediated and humoral immune responses to varicella-zoster virus. The relative contributions of humoral immunity and cell-mediated immunity to protection from varicella are unknown.

12.2 Pharmacodynamics

Transmission

In the placebo-controlled efficacy trial, transmission of vaccine virus was assessed in household settings (during the 8-week postvaccination period) in 416 susceptible placebo recipients who were household contacts of 445 vaccine recipients. Of the 416 placebo recipients, three developed varicella and seroconverted, nine reported a varicella-like rash and did not seroconvert, and six had no rash but seroconverted. If vaccine virus transmission occurred, it did so at a very low rate and possibly without recognizable clinical disease in contacts. These cases may represent either wild-type varicella from community contacts or a low incidence of transmission of vaccine virus from vaccinated contacts. Post-marketing experience suggests that transmission of varicella vaccine virus (Oka/Merck) resulting in varicella infection including disseminated disease may occur rarely between vaccine recipients (who develop or do not develop a varicella-like rash) and contacts susceptible to varicella including healthy as well as high risk individuals [see Warnings and Precautions (5.3)] {1,10}.

12.6 Duration of Protection

The duration of protection of VARIVAX is unknown; however, long-term efficacy studies have demonstrated continued protection up to 10 years after vaccination [see Clinical Studies (14.1)] {13}. A boost in antibody levels has been observed in vaccinees following exposure to wild-type varicella which could account for the apparent long-term protection after vaccination in these studies.

14 CLINICAL STUDIES

14.1 Clinical Efficacy

The protective efficacy of VARIVAX administered subcutaneously was established by: (1) a placebo-controlled, double-blind clinical trial, (2) comparing varicella rates in vaccinees versus historical controls, and (3) assessing protection from disease following household exposure.

Clinical Data in Children

One-Dose Regimen in Children

Although no placebo-controlled trial was carried out with VARIVAX using the current vaccine, a placebo-controlled trial was conducted using a formulation containing 17,000 PFU per dose {1,14}. In this trial, a single dose of VARIVAX protected 96 to 100% of children against varicella over a two-year period. The study enrolled healthy individuals 1 to 14 years of age (n=491 vaccine, n=465 placebo). In the first year, 8.5% of placebo recipients contracted varicella, while no vaccine recipient did, for a calculated protection rate of 100% during the first varicella season. In the second year, when only a subset of individuals agreed to remain in the blinded study (n=163 vaccine, n=161 placebo), 96% protective efficacy was calculated for the vaccine group as compared to placebo.

In early clinical trials, a total of 4240 children 1 to 12 years of age received 1000 to 1625 PFU of attenuated virus per dose of VARIVAX and have been followed for up to nine years post single-dose vaccination. In this group there was considerable variation in varicella rates among studies and study sites, and much of the reported data were acquired by passive follow-up. It was observed that 0.3 to 3.8% of vaccinees per year reported varicella (called breakthrough cases). This represents an approximate 83% (95% confidence interval [CI], 82%, 84%) decrease from the age-adjusted expected incidence rates in susceptible subjects over this same period {12}. In those who developed breakthrough varicella postvaccination, the majority experienced mild disease (median of the maximum number of lesions <50). In one study, a total of 47% (27/58) of breakthrough cases had <50 lesions compared with 8% (7/92) in unvaccinated individuals, and 7% (4/58) of breakthrough cases had >300 lesions compared with 50% (46/92) in unvaccinated individuals {15}.

Among a subset of vaccinees who were actively followed in these early trials for up to nine years postvaccination, 179 individuals had household exposure to varicella. There were no reports of breakthrough varicella in 84% (150/179) of exposed children, while 16% (29/179) reported a mild form of varicella (38% [11/29] of the cases with a maximum total number of <50 lesions; no individuals with >300 lesions). This represents an 81% reduction in the expected number of varicella cases utilizing the historical attack rate of 87% following household exposure to varicella in unvaccinated individuals in the calculation of efficacy.

In later clinical trials, a total of 1114 children 1 to 12 years of age received 2900 to 9000 PFU of attenuated virus per dose of VARIVAX and have been actively followed for up to 10 years post single-dose vaccination. It was observed that 0.2% to 2.3% of vaccinees per year reported breakthrough varicella for up to 10 years post single-dose vaccination. This represents an estimated efficacy of 94% (95% CI, 93%, 96%), compared with the age-adjusted expected incidence rates in susceptible subjects over the same period {1,12,16}. In those who developed breakthrough varicella postvaccination, the majority experienced mild disease, with the median of the maximum total number of lesions <50. The severity of reported breakthrough varicella, as measured by number of lesions and maximum temperature, appeared not to increase with time since vaccination.

Among a subset of vaccinees who were actively followed in these later trials for up to 10 years postvaccination, 95 individuals were exposed to an unvaccinated individual with wild-type varicella in a household setting. There were no reports of breakthrough varicella in 92% (87/95) of exposed children, while 8% (8/95) reported a mild form of varicella (maximum total number of lesions <50; observed range, 10 to 34). This represents an estimated efficacy of 90% (95% CI, 82%, 96%) based on the historical attack rate of 87% following household exposure to varicella in unvaccinated individuals in the calculation of efficacy.

Two-Dose Regimen in Children

In a clinical trial, a total of 2216 children 12 months to 12 years of age with a negative history of varicella were randomized to receive either 1 dose of VARIVAX (n=1114) or 2 doses of VARIVAX (n=1102) given 3 months apart. Subjects were actively followed for varicella, any varicella-like illness, or herpes zoster and any exposures to varicella or herpes zoster on an annual basis for 10 years after vaccination. Persistence of VZV antibody was measured annually for 9 years. Most cases of varicella reported in recipients of 1 dose or 2 doses of vaccine were mild {13}. The estimated vaccine efficacy for the 10-year observation period was 94% for 1 dose and 98% for 2 doses (p<0.001). This translates to a 3.4-fold lower risk of developing varicella >42 days postvaccination during the 10-year observation period in children who received 2 doses than in those who received 1 dose (2.2% vs. 7.5%, respectively).

Clinical Data in Adolescents and Adults

Two-Dose Regimen in Adolescents and Adults

In early clinical trials, a total of 796 adolescents and adults received 905 to 1230 PFU of attenuated virus per dose of VARIVAX and have been followed for up to six years following 2-dose vaccination. A total of 50 clinical varicella cases were reported >42 days following 2-dose vaccination. Based on passive follow-up, the annual varicella breakthrough event rate ranged from <0.1 to 1.9%. The median of the maximum total number of lesions ranged from 15 to 42 per year.

Although no placebo-controlled trial was carried out in adolescents and adults, the protective efficacy of VARIVAX was determined by evaluation of protection when vaccinees received 2 doses of VARIVAX 4 or 8 weeks apart and were subsequently exposed to varicella in a household setting. Among the subset of vaccinees who were actively followed in these early trials for up to six years, 76 individuals had household exposure to varicella. There were no reports of breakthrough varicella in 83% (63/76) of exposed vaccinees, while 17% (13/76) reported a mild form of varicella. Among 13 vaccinated individuals who developed breakthrough varicella after a household exposure, 62% (8/13) of the cases reported maximum total number of lesions <50, while no individual reported >75 lesions. The attack rate of unvaccinated adults exposed to a single contact in a household has not been previously studied. Utilizing the previously reported historical attack rate of 87% for wild-type varicella following household exposure to varicella among unvaccinated children in the calculation of efficacy, this represents an approximate 80% reduction in the expected number of cases in the household setting.

In later clinical trials, a total of 220 adolescents and adults received 3315 to 9000 PFU of attenuated virus per dose of VARIVAX and have been actively followed for up to six years following 2-dose vaccination. A total of 3 clinical varicella cases were reported >42 days following 2-dose vaccination. Two cases reported <50 lesions and none reported >75. The annual varicella breakthrough event rate ranged from 0 to 1.2%. Among the subset of vaccinees who were actively followed in these later trials for up to five years, 16 individuals were exposed to an unvaccinated individual with wild-type varicella in a household setting. There were no reports of breakthrough varicella among the exposed vaccinees.

There are insufficient data to assess the rate of protective efficacy of VARIVAX against the serious complications of varicella in adults (e.g., encephalitis, hepatitis, pneumonitis) and during pregnancy (congenital varicella syndrome).

14.2 Immunogenicity

In clinical trials, varicella antibodies have been evaluated following vaccination with formulations of VARIVAX containing attenuated virus ranging from 1000 to 50,000 PFU per dose in healthy individuals ranging from 12 months to 55 years of age {1,8}.

One-Dose Regimen in Children

In prelicensure efficacy studies, seroconversion was observed in 97% of vaccinees at approximately 4 to 6 weeks postvaccination in 6889 susceptible children 12 months to 12 years of age. Titers ≥5 gpELISA units/mL were induced in approximately 76% of children vaccinated with a single dose of vaccine at 1000 to 17,000 PFU per dose. Rates of breakthrough disease were significantly lower among children with VZV antibody titers ≥5 gpELISA units/mL compared with children with titers <5 gpELISA units/mL.

In an open label clinical trial (NCT00432523) 752 children 12 through 18 months of age received VARIVAX either intramuscularly (n=374) or subcutaneously (n=378), concomitantly with M-M-R II. Antibody responses to varicella virus were measured by gpELISA using sera obtained 6 weeks postvaccination. Seroresponse rate was defined as the percentage of initially seronegative children who achieved antibody titers above the seroresponse threshold for the assay 6 weeks post vaccination. The seroresponse threshold was defined as 5 gpELISA units for anti-varicella virus antibodies. Ninety-five percent of enrolled children were seronegative to varicella virus at baseline. In the pre-specified primary analysis, seroresponse rates to varicella virus were noninferior in the intramuscular group compared to the subcutaneous group (the lower bound of the 95% confidence interval for the difference in seroresponse rates [intramuscular group minus subcutaneous group] was ≥-10%). The proportions of children achieving antibody titers above the seroresponse thresholds for varicella virus were 88.4% (95% CI: 84.5, 91.6) of children in the intramuscular group and 85.5% (95% CI: 81.3, 89.0) of children in the subcutaneous.

Two-Dose Regimen in Children

In a multicenter study, 2216 healthy children 12 months to 12 years of age received either 1 dose or 2 doses of VARIVAX administered subcutaneously 3 months apart. The immunogenicity results are shown in Table 4.

Table 4: Summary of VZV Antibody Responses at 6 Weeks Postdose 1 and 6 Weeks Postdose 2 in Initially Seronegative Children 12 Months to 12 Years of Age (Vaccinations 3 Months Apart)
 | VARIVAX 1-Dose Regimen (N=1114) | VARIVAX 2-Dose Regimen (3 months apart) (N=1102)
 | 6 Weeks Postvaccination (n=892) | 6 Weeks Postdose 1 (n=851) | 6 Weeks Postdose 2 (n=769)
Seroconversion Rate | 98.9% | 99.5% | 99.9%
Percent with VZV Antibody Titer ≥5 gpELISA units/mL | 84.9% | 87.3% | 99.5%
Geometric mean titers in gpELISA units/mL (95% CI) | 12.0 (11.2, 12.8) | 12.8 (11.9, 13.7) | 141.5 (132.3, 151.3)
N = Number of subjects vaccinated.
n = Number of subjects included in immunogenicity analysis.

The results from this study and other studies in which a second dose of VARIVAX was administered 3 to 6 years after the initial dose demonstrate significant boosting of the VZV antibodies with a second dose. VZV antibody levels after 2 doses given 3 to 6 years apart are comparable to those obtained when the 2 doses are given 3 months apart.

Two-Dose Regimen in Adolescents and Adults

In a multicenter study involving susceptible adolescents and adults 13 years of age and older, 2 doses of VARIVAX administered subcutaneously 4 to 8 weeks apart induced a seroconversion rate of approximately 75% in 539 individuals 4 weeks after the first dose and of 99% in 479 individuals 4 weeks after the second dose. The average antibody response in vaccinees who received the second dose 8 weeks after the first dose was higher than that in vaccinees who received the second dose 4 weeks after the first dose. In another multicenter study involving adolescents and adults, 2 doses of VARIVAX administered subcutaneously 8 weeks apart induced a seroconversion rate of 94% in 142 individuals 6 weeks after the first dose and 99% in 122 individuals 6 weeks after the second dose.

14.3 Persistence of Immune Response

One-Dose Regimen in Children

In clinical studies involving healthy children who received 1 dose of VARIVAX subcutaneously, detectable VZV antibodies were present in 99.0% (3886/3926) at 1 year, 99.3% (1555/1566) at 2 years, 98.6% (1106/1122) at 3 years, 99.4% (1168/1175) at 4 years, 99.2% (737/743) at 5 years, 100% (142/142) at 6 years, 97.4% (38/39) at 7 years, 100% (34/34) at 8 years, and 100% (16/16) at 10 years postvaccination.

Two-Dose Regimen in Children

In recipients of 1 dose of VARIVAX administered subcutaneously over 9 years of follow-up, the geometric mean titers (GMTs) and the percent of subjects with VZV antibody titers ≥5 gpELISA units/mL generally increased. The GMTs and percent of subjects with VZV antibody titers ≥5 gpELISA units/mL in the 2-dose recipients were higher than those in the 1-dose recipients for the first year of follow-up and generally comparable thereafter. The cumulative rate of VZV antibody persistence with both regimens remained very high at year 9 (99.0% for the 1-dose group and 98.8% for the 2-dose group).

Two-Dose Regimen in Adolescents and Adults

In clinical studies involving healthy adolescents and adults who received 2 doses of VARIVAX subcutaneously, detectable VZV antibodies were present in 97.9% (568/580) at 1 year, 97.1% (34/35) at 2 years, 100% (144/144) at 3 years, 97.0% (98/101) at 4 years, 97.4% (76/78) at 5 years, and 100% (34/34) at 6 years postvaccination.

A boost in antibody levels has been observed in vaccinees following exposure to wild-type varicella, which could account for the apparent long-term persistence of antibody levels in these studies.

14.4 Studies with Other Vaccines

Concomitant Administration with M-M-R II

In combined clinical studies involving 1080 children 12 to 36 months of age, 653 children received VARIVAX and M-M-R II administered subcutaneously and concomitantly at separate injection sites and 427 received the vaccines six weeks apart. Seroconversion rates and antibody levels to measles, mumps, rubella, and varicella were comparable between the two groups at approximately six weeks postvaccination.

Concomitant Administration with Diphtheria and Tetanus Toxoids and Acellular Pertussis Vaccine Adsorbed (DTaP) and Oral Poliovirus Vaccine (OPV)

In a clinical study involving 318 children 12 months to 42 months of age, 160 received an investigational varicella-containing vaccine (a formulation combining measles, mumps, rubella, and varicella in one syringe) administered subcutaneously and concomitantly with booster doses of DTaP and OPV (no longer licensed in the United States). The comparator group of 144 children received M-M-R II concomitantly with booster doses of DTaP and OPV followed by VARIVAX administered subcutaneously six weeks later. At six weeks postvaccination, seroconversion rates for measles, mumps, rubella, and VZV and the percentage of vaccinees whose titers were boosted for diphtheria, tetanus, pertussis, and polio were comparable between the two groups. Anti-VZV levels were decreased when the investigational vaccine containing varicella was administered concomitantly with DTaP {17}. No clinically significant differences were noted in adverse reactions between the two groups.

Concomitant Administration with PedvaxHIB

In a clinical study involving 307 children 12 to 18 months of age, 150 received an investigational varicella-containing vaccine (a formulation combining measles, mumps, rubella, and varicella in one syringe) administered subcutaneously and concomitantly with a booster dose of PedvaxHIB [Haemophilus b Conjugate Vaccine (Meningococcal Protein Conjugate)], while 130 received M-M-R II concomitantly with a booster dose of PedvaxHIB followed by VARIVAX administered subcutaneously 6 weeks later. At six weeks postvaccination, seroconversion rates for measles, mumps, rubella, and VZV, and GMTs for PedvaxHIB were comparable between the two groups. Anti-VZV levels were decreased when the investigational vaccine containing varicella was administered concomitantly with PedvaxHIB {18}. No clinically significant differences in adverse reactions were seen between the two groups.

Concomitant Administration with M-M-R II and COMVAX

In a clinical study involving 822 children 12 to 15 months of age, 410 received COMVAX [Haemophilus b Conjugate (Meningococcal Protein Conjugate) and Hepatitis B (Recombinant) Vaccine] (no longer licensed in the US), M-M-R II, and VARIVAX concomitantly at separate injection sites, and 412 received COMVAX followed by M-M-R II and VARIVAX given concomitantly at separate injection sites, 6 weeks later. In this study VARIVAX was administered subcutaneously. At 6 weeks postvaccination, the immune responses for the subjects who received the concomitant doses of COMVAX, M-M-R II, and VARIVAX were similar to those of the subjects who received COMVAX followed 6 weeks later by M-M-R II and VARIVAX with respect to all antigens administered. There were no clinically important differences in reaction rates when the three vaccines were administered concomitantly versus six weeks apart.

15 REFERENCES

1. Weibel, R.E.; et al.: Live Attenuated Varicella Virus Vaccine. Efficacy Trial in Healthy Children. N Engl J Med. 310(22): 1409-1415, 1984.
2. Arbeter, A.M.; et al.: Varicella Vaccine Trials in Healthy Children. A Summary of Comparative and Follow-up Studies. Am J Dis Child. 138: 434-438, 1984.
3. Weibel, R.E.; et al.: Live Oka/Merck Varicella Vaccine in Healthy Children. Further Clinical and Laboratory Assessment. JAMA. 254(17): 2435-2439, 1985.
4. Chartrand, D.M.; et al.: New Varicella Vaccine Production Lots in Healthy Children and Adolescents. Abstracts of the 1988 Inter-Science Conference Antimicrobial Agents and Chemotherapy: 237(Abstract #731).
5. Johnson, C.E.; et al.: Live Attenuated Varicella Vaccine in Healthy 12- to 24-Month-Old Children. Pediatrics. 81(4): 512-518, 1988.
6. Gershon, A.A.; et al.: Immunization of Healthy Adults with Live Attenuated Varicella Vaccine. J Infect Dis. 158(1): 132-137, 1988.
7. Gershon, A.A.; et al.: Live Attenuated Varicella Vaccine: Protection in Healthy Adults Compared with Leukemic Children. J Infect Dis. 161: 661-666, 1990.
8. White, C.J.; et al.: Varicella Vaccine (VARIVAX) in Healthy Children and Adolescents: Results From Clinical Trials, 1987 to 1989. Pediatrics. 87(5): 604-610, 1991.
9. Peter, G.; et al (eds): Report of the Committee on Infectious Diseases, Twenty-fourth Edition, American Academy of Pediatrics, 344-357, 1997.
10. Galea, S.; et al.: The Safety Profile of Varicella Vaccine: A 10-Year Review. J Infect Dis. 197(S2): 165-169, 2008.
11. Hammerschlag, M.R.; et al.: Herpes Zoster in an Adult Recipient of Live Attenuated Varicella Vaccine. J Infect Dis. 160(3): 535-537, 1989.
12. Guess, H.A.; et al.: Population-Based Studies of Varicella Complications. Pediatrics. 78(suppl): 723-727, 1986.
13. Kuter, B.J.; et al.: Ten Year Follow-up of Healthy Children who Received One or Two Injections of Varicella Vaccine. Pediatr Infect Dis J. 23: 132-37, 2004.
14. Kuter, B.J.; et al.: Oka/Merck Varicella Vaccine in Healthy Children: Final Report of a 2-Year Efficacy Study and 7-Year Follow-up Studies. Vaccine. 9: 643-647, 1991.
15. Bernstein, H.H.; et al.: Clinical Survey of Natural Varicella Compared with Breakthrough Varicella After Immunization with Live Attenuated Oka/Merck Varicella Vaccine. Pediatrics. 92(6): 833-837, 1993.
16. Wharton, M.: The Epidemiology of Varicella-zoster Virus Infections. Infect Dis Clin North Am. 10(3):571-581, 1996.
17. White, C.J. et al.: Measles, Mumps, Rubella, and Varicella Combination Vaccine: Safety and Immunogenicity Alone and in Combination with Other Vaccines Given to Children. Clin Infect Dis. 24(5): 925-931, 1997.
18. Reuman, P.D.; et al.: Safety and Immunogenicity of Concurrent Administration of Measles-Mumps-Rubella-Varicella Vaccine and PedvaxHIB® Vaccines in Healthy Children Twelve to Eighteen Months Old. Pediatr Infect Dis J. 16(7): 662-667, 1997.

16 HOW SUPPLIED/STORAGE AND HANDLING

VARIVAX is supplied as follows:

(1) a box of 10 single-dose vials of lyophilized vaccine (package A), NDC 0006-4827-00
(2) a box of 10 prefilled syringes of sterile diluent, NDC 0006-4175-88 (package B) OR a box of 10 vials of sterile diluent, NDC 0006-4309-00 (package B)

Storage

Vaccine Vial

During shipment, maintain the vaccine at a temperature between –58°F and +5°F (–50°C and –15°C). Use of dry ice may subject VARIVAX to temperatures colder than –58°F (–50°C).

Before reconstitution, store the lyophilized vaccine in a freezer at a temperature between –58°F and +5°F (–50°C and –15°C). Any freezer (e.g., chest, frost-free) that reliably maintains an average temperature between –58°F and +5°F (–50°C and –15°C) and has a separate sealed freezer door is acceptable for storing VARIVAX. Routine defrost cycling of a frost-free freezer is acceptable.

VARIVAX may be stored at refrigerator temperature (36°F to 46°F, 2°C to 8°C) for up to 72 continuous hours prior to reconstitution. Vaccine stored at 2°C to 8°C which is not used within 72 hours of removal from +5°F (–15°C) storage should be discarded.

Before reconstitution, protect from light.

Sterile Diluent

The sterile diluent should be stored at room temperature (68°F to 77°F, 20°C to 25°C), or in the refrigerator.

DISCARD IF RECONSTITUTED VACCINE IS NOT USED WITHIN 30 MINUTES.

For information regarding the product or questions regarding storage conditions, call 1-800-9-VARIVAX (1-800-982-7482).

17 PATIENT COUNSELING INFORMATION

Advise the patient to read the FDA-approved patient labeling (Patient Information).

Discuss the following with the patient:

- Question the patient, parent, or guardian about reactions to previous vaccines.
- Provide a copy of the patient information (PPI) located at the end of this insert and discuss any questions or concerns.
- Inform patient, parent, or guardian that vaccination with VARIVAX may not result in protection of all healthy, susceptible children, adolescents, and adults.
- Inform female patients to avoid pregnancy for three months following vaccination.
- Inform patient, parent, or guardian of the benefits and risks of VARIVAX.
- Instruct patient, parent, or guardian to report any adverse reactions or any symptoms of concern to their healthcare professional.

The U.S. Department of Health and Human Services has established a Vaccine Adverse Event Reporting System (VAERS) to accept all reports of suspected adverse events after the administration of any vaccine. For information or a copy of the vaccine reporting form, call the VAERS toll-free number at 1-800-822-7967, or report online at www.vaers.hhs.gov .

Dist. by: Merck Sharp & Dohme LLC
Rahway, NJ 07065, USA

For patent information: www.msd.com/research/patent

Copyright © 1995-2023 Merck & Co., Inc., Rahway, NJ, USA, and its affiliates.
All rights reserved.

uspi-v210-i-fro-2308r723

Patient Information
VARIVAX® (pronounced "VAR ih vax")
Varicella Virus Vaccine Live

This is a summary of information about VARIVAX®. You should read it before you or your child get the vaccine. If you have any questions about the vaccine after reading this leaflet, you should ask your healthcare professional. This is a summary only. It does not take the place of talking about VARIVAX with your doctor, nurse, or other healthcare professional. Only your healthcare professional can decide if VARIVAX is right for you or your child.

What is VARIVAX and how does it work?

VARIVAX is also known as Varicella Virus Vaccine Live. It is a live virus vaccine that is given as a shot. It is meant to help prevent chickenpox. Chickenpox is sometimes called varicella (pronounced VAR ih sell a).

VARIVAX contains a weakened form of chickenpox virus.

VARIVAX works by helping the immune system protect you or your child from getting chickenpox.

VARIVAX may not protect everyone who gets it.

VARIVAX does not treat chickenpox once you or your child have it.

What do I need to know about chickenpox?

Chickenpox is an illness that occurs most often in children who are 5 to 9 years old. It can be passed to others. The illness can include headache, fever, and general discomfort. Then an itchy rash occurs, which can turn into blisters. The most common complication is that the blisters can get infected. Less common but very serious complications can occur. These include pneumonia, inflammation of the brain, Reye syndrome (which affects the liver and the brain), and death. Severe disease and serious complications are more likely to occur in adolescents and adults.

Who should not get VARIVAX?

Do not get VARIVAX if you or your child:

- are allergic to any of its ingredients. (This includes gelatin or neomycin. See the ingredient list at the end of this leaflet.)
- have a weakened immune system (which includes taking high doses of steroids by mouth or in a shot).
- have a fever.
- have active tuberculosis that is not treated.
- are pregnant or plan to get pregnant within the next three months.

What should I tell my healthcare professional before getting VARIVAX?

Tell your healthcare professional if you or your child:

- have or have had any medical problems.
- have received blood or plasma transfusions or human serum globulin.
- take any medicines. (This includes non-prescription medicines and dietary supplements.)
- have any allergies. (This includes allergies to neomycin or gelatin.)
- had an allergic reaction to any other vaccine.

How is VARIVAX given?

VARIVAX is given as a shot to people who are 12 months old or older. If your child is 12 months to 12 years old and your doctor gives a second dose, the second dose must be given at least 3 months after the first shot.

A second dose should be given to those who first get the vaccine when they are 13 years old or older. This second dose should be given 4 to 8 weeks after the first dose.

Your doctor or healthcare professional will use the official recommendations to decide the number of shots needed and when to get them.

If a dose is missed, your healthcare professional will let you know when you should have it.

What should you or your child avoid when getting VARIVAX?

Do not take aspirin or aspirin-containing products for 6 weeks after getting VARIVAX.

In rare circumstances, it is possible to catch chickenpox, including severe chickenpox, from a person who has been vaccinated with VARIVAX. This may occur in persons who have not previously been vaccinated or had chickenpox, as well as persons who fall into one of the following categories:

- people who have a weakened immune system.
- pregnant women who have never had chickenpox.
- newborn babies whose mothers have never had chickenpox.
- newborn babies born at less than 28 weeks of pregnancy.

Whenever possible, individuals who have been vaccinated with VARIVAX should attempt to avoid close contact for up to six weeks following the vaccination, with anyone who falls into one of the categories above. Tell your doctor or healthcare professional if you or your child expect to have close contact with someone who falls into one of these groups.

What are the possible side effects of VARIVAX?

The most common side effects reported after taking VARIVAX are:

- Fever
- Pain, swelling, itching, or redness at the site of the shot
- Chickenpox-like rash on the body or at the site of the shot
- Irritability

Other less common side effects have also been reported.

- Tingling of the skin
- Shingles (herpes zoster)

Tell your healthcare professional if you have any of the following problems within a short time after getting VARIVAX because they may be signs of an allergic reaction:

- Shortness of breath or wheezing
- Rash or hives

Other side effects have been reported. Some of them were serious. These include bruising more easily than normal; red or purple, flat, pinhead spots under the skin; severe paleness; difficulty walking; severe skin disorders; skin infection; and chickenpox. Rarely, swelling of the brain (encephalitis), stroke, inflammation of the coverings of the brain and spinal cord (meningitis), inflammation of the lungs (known as pneumonia or pneumonitis), and seizures with or without a fever have been reported. It is not known if these rare side effects are related to the vaccine.

Your doctor has a more complete list of side effects for VARIVAX.

Tell your doctor or healthcare professional if you or your child have any new or unusual symptoms after getting VARIVAX.

Report the following to your doctor or your child's doctor:

- any adverse reactions following vaccination
- exposure to VARIVAX during pregnancy
- exposure to VARIVAX during the 3 months before getting pregnant.

You may also report these events to Merck Sharp & Dohme LLC at 1-877-888-4231, or directly to the Vaccine Adverse Event Reporting System (VAERS). The VAERS toll-free number is 1-800-822-7967 or report online to www.vaers.hhs.gov .

What are the ingredients of VARIVAX?

Active Ingredient: a weakened form of chickenpox virus.

Inactive Ingredients: sucrose, hydrolyzed gelatin, sodium chloride, monosodium L-glutamate, sodium phosphate dibasic, potassium phosphate monobasic, potassium chloride, residual components of MRC-5 cells including DNA and protein, sodium phosphate monobasic, EDTA, neomycin, fetal bovine serum.

What else should I know about VARIVAX?

This leaflet summarizes important information about VARIVAX.

If you would like more information, talk to your healthcare professional, or call 1-800-637-2590.

Dist. by: Merck Sharp & Dohme LLC
Rahway, NJ 07065, USA

For patent information: www.msd.com/research/patent

Copyright © 1995-2023 Merck & Co., Inc., Rahway, NJ, USA, and its affiliates.
All rights reserved.

usppi-v210-i-fro-2303r712

PACKAGE LABEL

PRINCIPAL DISPLAY PANEL - 1 Single Dose 0.5 mL Vial Carton

NDC 0006-4826-00

1 Single-dose 0.5-mL Vial

VARICELLA VIRUS VACCINE
LIVE
VARIVAX®

STORE FROZEN

Oka/Merck Strain. Human cell
tissue culture origin containing
trace quantities of neomycin.
Contains no preservatives.

Rx only

A

PRINCIPAL DISPLAY PANEL - 10 Single Dose 0.5 mL Vial Carton

10 Single-dose 0.5-mL Vials
NDC 0006-4827-00

VARICELLA VIRUS VACCINE LIVE
VARIVAX®

STORE FROZEN

Oka/Merck Strain. Human cell tissue culture
origin containing trace quantities of neomycin.
Contains no preservatives.

Rx only

A